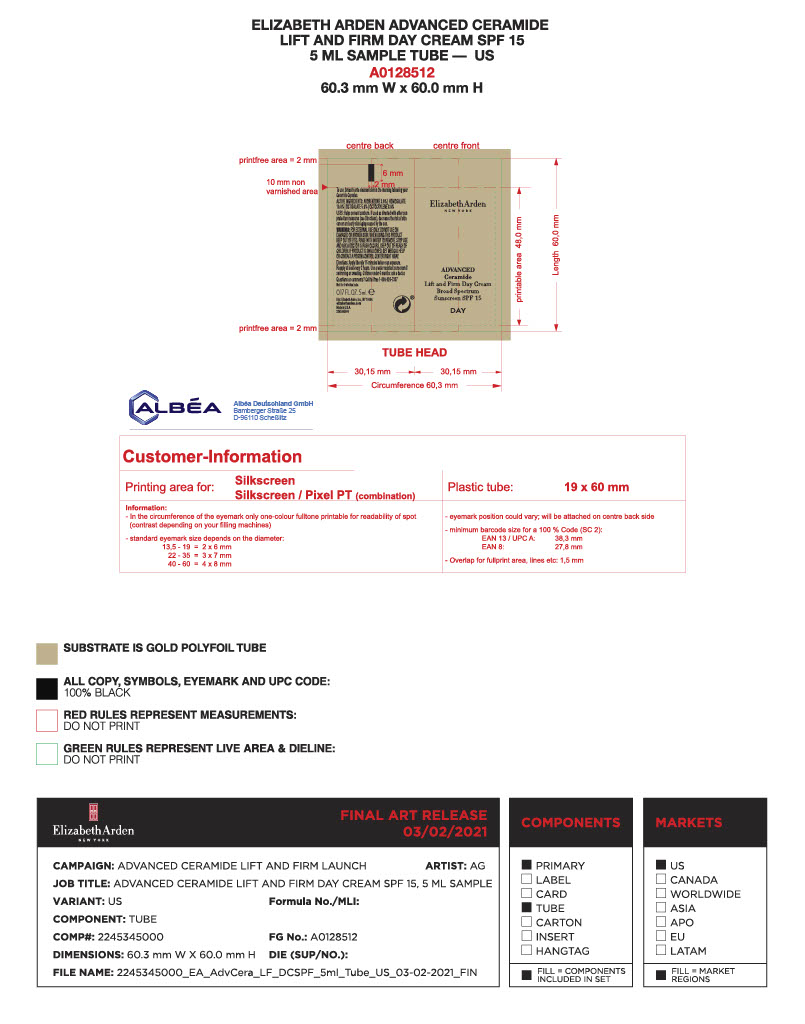 DRUG LABEL: Advanced Ceramide Lift and Firm Day Cream
NDC: 10967-689 | Form: EMULSION
Manufacturer: REVLON
Category: otc | Type: HUMAN OTC DRUG LABEL
Date: 20241231

ACTIVE INGREDIENTS: HOMOSALATE 100 mg/1 g; OCTOCRYLENE 80 mg/1 g; AVOBENZONE 30 mg/1 g; OCTISALATE 50 mg/1 g
INACTIVE INGREDIENTS: HYALURONATE SODIUM; POLYMETHYLSILSESQUIOXANE (4.5 MICRONS); ACETYL TETRAPEPTIDE-9; LEONTOPODIUM NIVALE SUBSP. ALPINUM WHOLE; ACETYL TETRAPEPTIDE-11; CARBOMER INTERPOLYMER TYPE A (ALLYL SUCROSE CROSSLINKED); HEXYLENE GLYCOL; ETHYLHEXYL PALMITATE; CERAMIDE NP; WATER; TROMETHAMINE; CAPRYLYL GLYCOL; CHOLESTEROL; GLYCERIN; PEG-100 STEARATE; EDETATE DISODIUM ANHYDROUS; BUTYLENE GLYCOL; DIMETHICONE; PHYTOSPHINGOSINE; XANTHAN GUM; PHENOXYETHANOL; CARBOMER HOMOPOLYMER, UNSPECIFIED TYPE; CHLORPHENESIN; SEA SALT; POLYSORBATE 60; POLYSORBATE 20; CERAMIDE AP; STYRENE/ACRYLAMIDE COPOLYMER (MW 500000); GLYCERYL MONOSTEARATE; C12-20 ALKYL GLUCOSIDE; DIMETHYL ISOSORBIDE; 2-ETHYLHEXYL ACRYLATE, METHACRYLATE, METHYL METHACRYLATE, OR BUTYL METHACRYLATE/HYDROXYPROPYL DIMETHICONE COPOLYMER (30000-300000 MW); SILICA DIMETHYL SILYLATE; C14-22 ALCOHOLS; HYDROXYETHYL ACRYLATE/SODIUM ACRYLOYLDIMETHYL TAURATE COPOLYMER (45000 MPA.S AT 1%); ISOHEXADECANE; SODIUM LAUROYL LACTYLATE; CERAMIDE 1; ALPHA-TOCOPHEROL ACETATE; CARRAGEENAN SODIUM

Elizabeth Arden Advanced Ceramide Lift and Firm Day Cream
Broad-Spectrum Sunscreen SPF 15

ACTIVE INGREDIENTS

AVOBENZONE 3.00%

HOMOSALATE 10.0%

OCTISALATE 5.0%

OCTOCRYLENE 8.0%

OTHER INGREDIENTS

WATER/AQUA/EAU, GLYCERIN, HEXYLENE GLYCOL, DIMETHICONE, C14-22 ALCOHOLS, PEG-100 STEARATE, GLYCERYL STEARATE, STYRENE/ACRYLATES COPOLYMER, ACRYLATES/DIMETHICONE COPOLYMER, POLYMETHYLSILSESQUIXANE, ACETYL TETRAPEPTIDE-11, ACETYL TETRAPEPTIDE-9, ACRYLATES/C10-30 ALKYL ACRYLATE CROSSPOLYMER, AMMONIUM HYDROXIDE, BUTYLENE GLYCOL, C12-20 ALKYL GLUCOSIDE, CAPRYLYL GLYCOL, CARBOMER, CERAMIDE AP, CERAMIDE EOP, CERAMIDE NP, CHOLESTEROL, DIMETHYL ISOSORBIDE, DISODIUM EDTA, ETHLYHEXYL PALMITATE, HYDROXYETHYL ACRYLATE/SODIUM ACRYLOYLDIMETHYL, TAURATE COPOLYMER, ISOHEXADECANE, LEONTOPODIUM ALPINUM CALLUS CULTURE EXTRACT, MARIS SAL/SEA SALT/SEL MARIN, PHYTOSPHINGOSINE, POLYSORBATE 20, POLYSORBATE 60, SILICA DIMETHYL SILYLATE, SODIUM CARRAGEENAN, SODIUM HYALURONATE, SODIUM LAUROYL LACTYLATE, TOCOPHERYL ACETATE, TROMETHAMINE, XANTHAM GUM, FRAGRANCE, CHLORPHENESIN, PHENOXYETHANOL.

USES

- Helps prevent sunburn
- if used as directed with other sun protection measures (see Directions), decreases the risk of skin cancer and early skin aging caused by the sun.

WARNINGS

- For external use only
- Do not use on damaged or broken skin
- When using this product keep out of eyes. Rinse with water to remove.
- Stop use and ask a doctor if rash occurs
- keep out of reach of children.

If product is swallowed, get medical help or contact a Poison Control Center right away.

DIRECTIONS

- Apply liberally 15 minutes before sun exposure
- Reapply:

- at least every 2 hours

- Sun Protection Measures. Spending time in the sun increases your risk of skin cancer and early skin aging. To decrease this risk, regularly use a sunscreen with a broad spectrum SPF of 15 or higher and other sun protection measures including:

- Limit time in the sun, especially from 10 a.m. - 2 p.m.

- Wear long-sleeve shirts, pants, hats, and sunglasses

- Use a water resistant sunscreen if swimming or sweating
- Children under 6 months: Ask a doctor.

DOSAGE AND ADMINISTRATION

Apply liberally 15 minutes before sun exposure.

KEEP OUT OF REACH OF CHILDREN

Keep out of the reach of children. If product is swallowed, get medical help or contact a Poison Control Center right away.

PURPOSE

Sunscreen

INDICATIONS AND USAGE

Helps prevent sunbunrs. If used as directed with other sun protection measures (See Directions), decreases the risk of skin cancer and early skin aging caused by the sun.